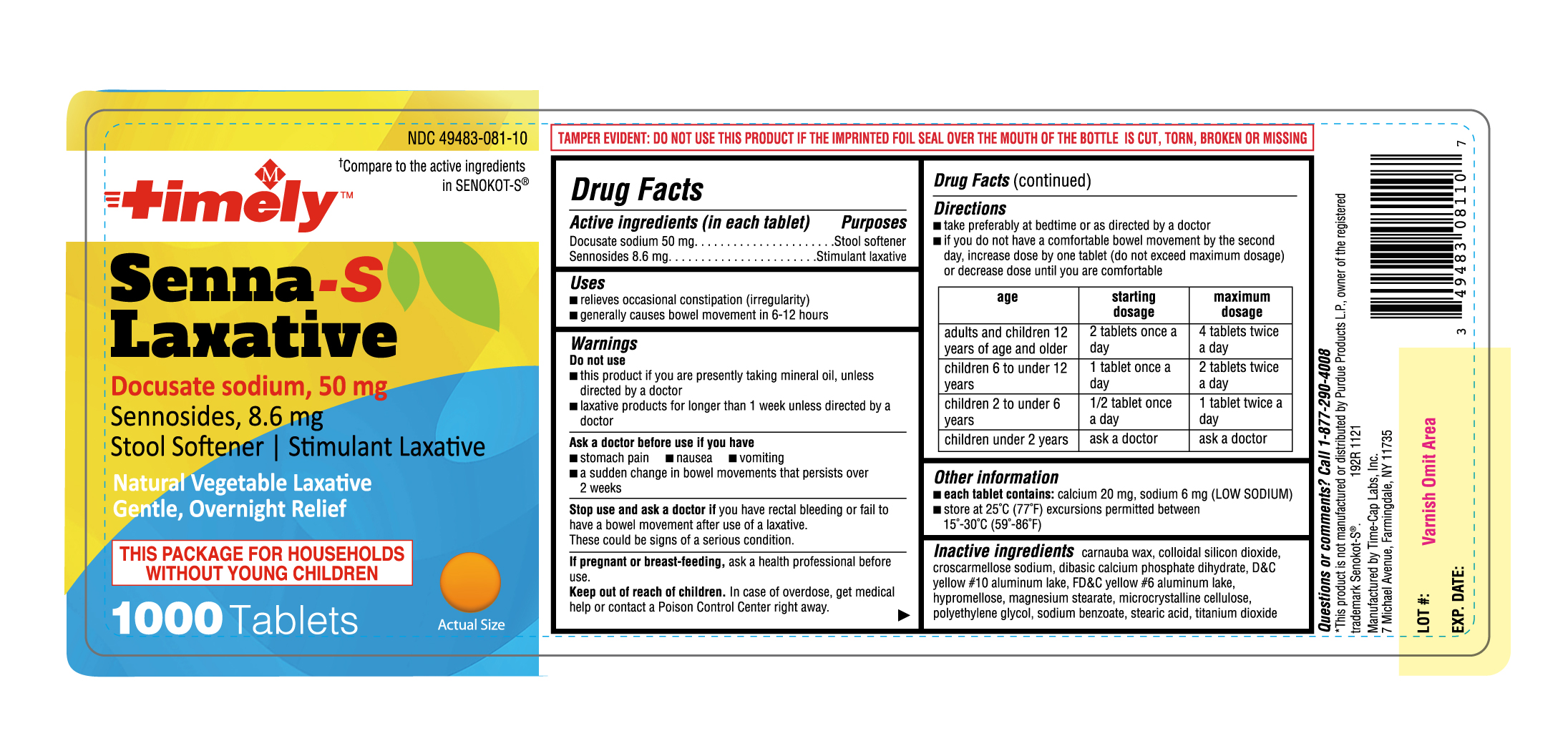 DRUG LABEL: SENNA TIME S
NDC: 49483-081 | Form: TABLET, FILM COATED
Manufacturer: TIME CAP LABORATORIES, INC
Category: otc | Type: HUMAN OTC DRUG LABEL
Date: 20250208

ACTIVE INGREDIENTS: DOCUSATE SODIUM 50 mg/1 1; SENNOSIDES A AND B 8.6 min/1 1
INACTIVE INGREDIENTS: CARNAUBA WAX; SILICON DIOXIDE; D&C YELLOW NO. 10 ALUMINUM LAKE; FD&C YELLOW NO. 6 ALUMINUM LAKE; HYPROMELLOSES; MAGNESIUM STEARATE; CELLULOSE, MICROCRYSTALLINE; POLYETHYLENE GLYCOL; SODIUM BENZOATE; STEARIC ACID; TITANIUM DIOXIDE; CROSCARMELLOSE SODIUM; DIBASIC CALCIUM PHOSPHATE DIHYDRATE

192R Timely 49483 081 Docusate sodium 50 mg Sennosides 8.6 mg tablets

Active ingredients (in each tablet)

Docustate sodium 50 mg

Sennosides 8.6 mg

Purposes

Stool softener

Stimulant laxative

Uses

- relieves occasional constipation (irregularity)
- generally causes bowel movement in 6-12 hours

Warnings

Do not use

- this product if you are presently taking mineral oil, unless directed by a doctor
- laxative products for longer than 1 week unless directed by a doctor

Ask a doctor before use if you have

- stomach pain
- nausea
- vomiting
- a sudden change in bowel movements that persists over 2 weeks

Stop use and ask a doctor if you have rectal bleeding or fail to have a bowel movement after use of a laxative.

These could be signs of a serious condition

PREGNANCY OR BREAST FEEDING

If pregnant or breast-feeding, ask a health professional before use.

KEEP OUT OF REACH OF CHILDREN

Keep out of the reach of children. In case of overdose, get medical help or contact a Poison Control Center right away.

Directions

- take preferably at bedtime or as directed by a doctor.
- if you do not have a comfortable bowel movement by the second day, increase dose by one tablet (do not exceed maximum dosage) or decrease dose until you are comfortable

age | starting dosage | maximum dosage
adults and children 12 years of age and older | 2 tablets once a day | 4 tablets twice a day
children 6 to under 12 years | 1 tablet once a day | 2 tablets twice a day
children 2 to under 6 years | ½ tablet once a day | 1 tablet twice a day
children under 2 years | ask a doctor | ask a doctor

Other information

- each tablet contains: calcium 20 mg, sodium 6 mg (LOW SODIUM)
- store at 25°C (77°F) excursions permitted between 15°-30°C (59°-86°F)

INACTIVE INGREDIENT

Inactive ingredients carnauba wax, colloidal silicon dioxide, croscarmellose sodium, dibasic calcium phosphate dihydrate, D&C yellow#10 aluminum lake, FD&C yellow #6 aluminum lake, hypromellose, magnesium stearate, microcrystalline cellulose, polyethylene glycol, sodium benzoate, stearic acid, titanium dioxide

Questions or comments?

Call 1-877-290-4008